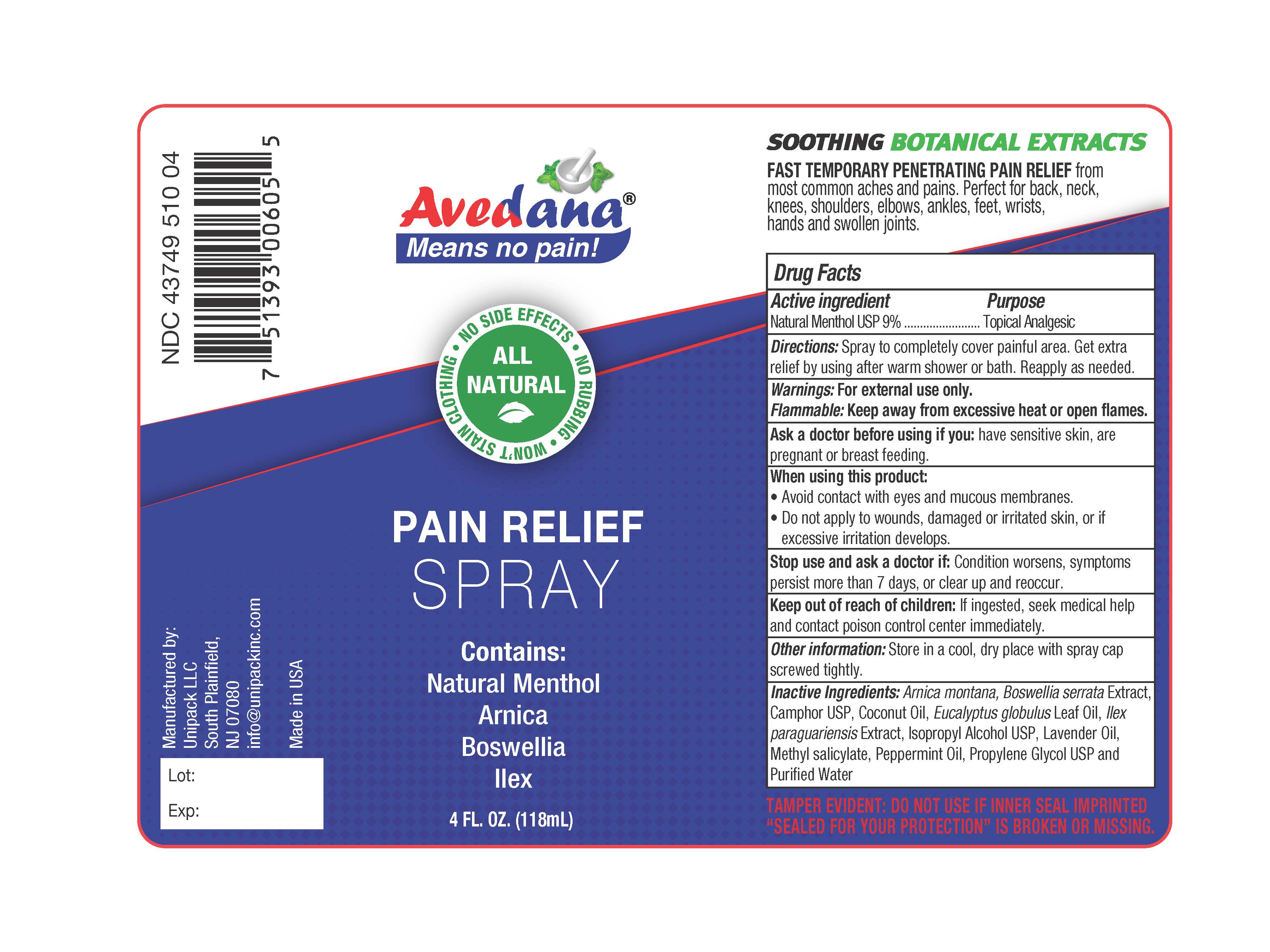 DRUG LABEL: Avedana Pain Relief
NDC: 43749-510 | Form: SPRAY
Manufacturer: Unipack LLC
Category: otc | Type: HUMAN OTC DRUG LABEL
Date: 20240104

ACTIVE INGREDIENTS: MENTHOL 9 g/100 mL
INACTIVE INGREDIENTS: FD&C BLUE NO. 1; ISOPROPYL ALCOHOL; PEPPERMINT OIL; COCONUT OIL; METHYL SALICYLATE; ARNICA MONTANA; PROPYLENE GLYCOL; ILEX PARAGUARIENSIS LEAF; LAVENDER OIL; BOSWELLIA SERRATA RESIN OIL; WATER; CAMPHOR (SYNTHETIC); EUCALYPTUS OIL

Avedana® Pain Relief Spray

Active ingredients

Active ingredients Purpose
Natural Menthol USP 9%....................................................Topical Analgesic

Purpose

Active ingredients Purpose
Natural Menthol USP 9%....................................................Topical Analgesic

Directions

Directions: Spray to completely cover painful area. Get extra relief by using after warm shower or bath. Reapply as needed.

Warnings

For external use only.

Flammable

Keep away from excessive heat or open flames.

Ask a doctor before using if you: have sensitive skin, are pregnant or are breast feeding.

When using this product:

-Avoid contact with eyes and mucous membranes.

-Do not apply to wounds, damaged or irritated skin, or if excessive irritation develops.

Stop use and ask a doctor if: condition worsens, symptoms persist more than 7 days, or clear up and reoccur.

Keep out of reach of children: If ingested, seek medical help and contact poison control center immediately.

Other information

Store in a cool, dry place with spray cap screwed tightly.

Inactive Ingredients:

Inactive Ingredients: Arnica montana, Boswellia serrata Extract, Camphor USP, Coconut Oil, Eucalyptus globulus Leaf Oil, Ilex paraguariensis Extract, Isopropyl Alcohol USP, Lavender Oil, Methyl salicylate, Peppermint Oil, Propylene Glycol USP, and Purified Water

Directions

Directions: Spray to completely cover painful area. Get extra relief by using after warm shower or bath. Reapply as needed.

Avedana® Pain Relieving Spray

Made with All - Natural Botanical Ingrdeints.